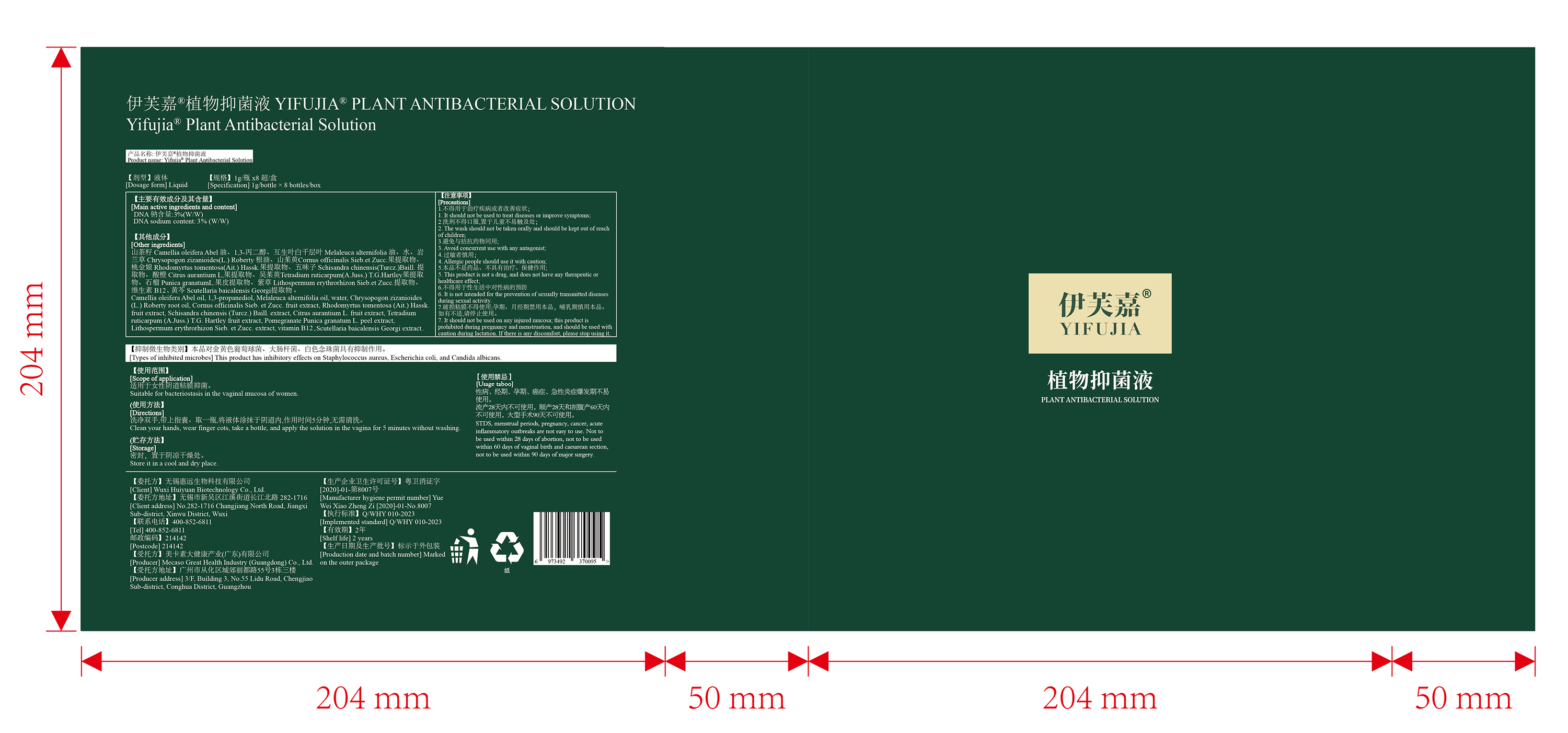 DRUG LABEL: YIFUJIA PLANT ANTIBACTERIAL Solution
NDC: 84341-001 | Form: LIQUID
Manufacturer: Mecaso Great Health Industry (Guangdong) Co.,Ltd.
Category: otc | Type: HUMAN OTC DRUG LABEL
Date: 20240521

ACTIVE INGREDIENTS: DEOXYRIBONUCLEIC ACID (PLASMID PUB110) 3 g/100 g
INACTIVE INGREDIENTS: POMEGRANATE FRUIT RIND; LITHOSPERMUM ERYTHRORHIZON ROOT; VETIVER OIL; PROPANEDIOL; TEA TREE OIL; RHODOMYRTUS TOMENTOSA FRUIT; WATER; SCHISANDRA CHINENSIS FRUIT; SCUTELLARIA BAICALENSIS ROOT; CYANOCOBALAMIN; TETRADIUM RUTICARPUM FRUIT; CORNUS OFFICINALIS FRUIT; TANGERINE PEEL; CAMELLIA OIL

YIFUJIA PLANT ANTIBACTERIAL SOLUTION

ACTIVE INGREDIENT

DNA sodium content: 3%

PURPOSE

This product has inhibitory effects on Staphylococcus aureus, Escherichia coli, and Candida albicans.

KEEP OUT OF REACH OF CHILDREN SECTION

INDICATIONS AND USAGE

Suitable for bacteriostasis in the vaginal mucosa of women

WARNINGS

1. It should not be used to treat diseases or improve symptoms.
2. The wash should not be taken orally and should be kept out of reach.
3. Avoid concurrent use with any antagonist.
4. Allergic people should use it with caution.
5. This product is not a drug, and does not have any therapeutic or healthcare effect.
6. It is not intended for the prevention of sexually transmitted diseases during sexual activity.
7. It should not be used on any injured mucosa; this product is prohibited during pregnancy and menstruation, and should be used withcaution during lactation. If there is any discomfort, please stop using it.
STDS, menstrual periods, pregnancy, cancer, acuteinflammatory outbreaks are not easy to use. Not tobe used within 28 days of abortion, not to be usedwithin 60 days of vaginal birth and caesarean section,not to be used within 90 days of major surgery

DOSAGE AND ADMINISTRATION

Clean your hands, wear finger cots, take a bottle, and apply the solution in the vagina for 5 minutes without washing.

STORAGE AND HANDLING

Store it in a cool and dry place.

INACTIVE INGREDIENT

Camellia oleifera Abel oil
PROPANEDIOL
MELALEUCA ALTERNIFOLIA (TEA TREE) LEAF OIL
VETIVERIA ZIZANIOIDES ROOT OIL
CORNUS OFFICINALIS FRUIT EXTRACT
RHODOMYRTUS TOMENTOSA FRUIT EXTRACT
SCHISANDRA CHINENSIS EXTRACT [WHO-DD]
CITRUS AURANTIUM TACHIBANA FRUIT EXTRACT
Tetradium ruticarpum(A.Juss.) T.G.Hartley FRUIT EXTRACT
PUNICA GRANATUM PERICARP EXTRACT
LITHOSPERMUM ERYTHRORHIZON EXTRACT
SCUTELLARIA BAICALENSIS EXTRACT
CYANOCOBALAMIN
WATER